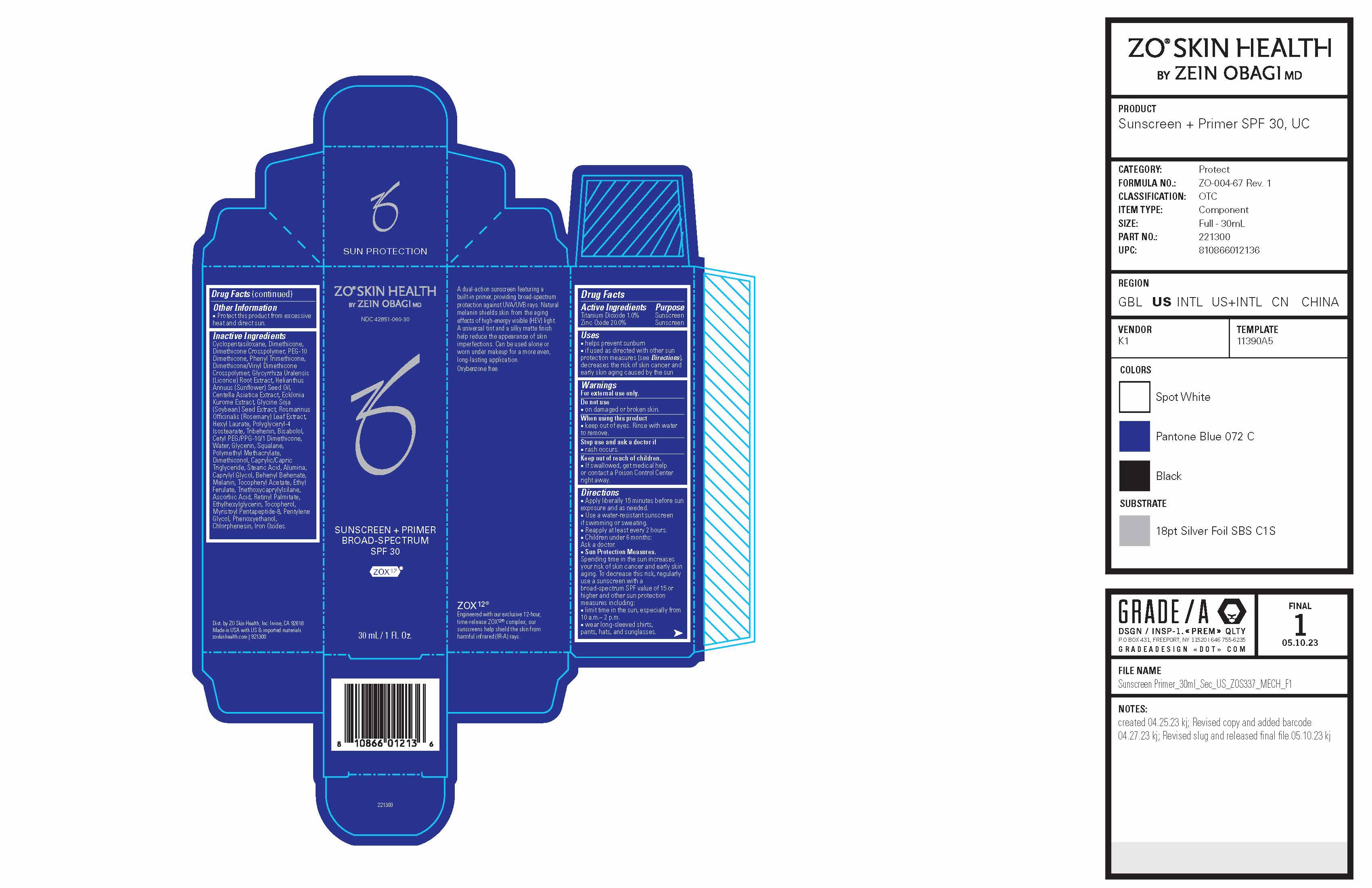 DRUG LABEL: ZO Skin Health Sunscreen Plus Primer Broad-Spectrum SPF 30
NDC: 42851-060 | Form: CREAM
Manufacturer: ZO Skin Health, Inc.
Category: otc | Type: HUMAN OTC DRUG LABEL
Date: 20241029

ACTIVE INGREDIENTS: TITANIUM DIOXIDE 10 mg/1 mL; ZINC OXIDE 200 mg/1 mL
INACTIVE INGREDIENTS: SOYBEAN; ROSEMARY; HEXYL LAURATE; POLYGLYCERYL-4 ISOSTEARATE; TRIBEHENIN; WATER; GLYCERIN; SQUALANE; ALPHA-TOCOPHEROL ACETATE; STEARIC ACID; CAPRYLYL GLYCOL; BEHENYL BEHENATE; ETHYL FERULATE; TRIETHOXYCAPRYLYLSILANE; ASCORBIC ACID; VITAMIN A PALMITATE; ETHYLHEXYLGLYCERIN; TOCOPHEROL; PENTYLENE GLYCOL; PHENOXYETHANOL; CHLORPHENESIN; CYCLOMETHICONE 5; LEVOMENOL; CETYL PEG/PPG-10/1 DIMETHICONE (HLB 2); FERRIC OXIDE RED; ALUMINUM OXIDE; MEDIUM-CHAIN TRIGLYCERIDES; DIMETHICONE; PEG-10 DIMETHICONE (600 CST); PHENYL TRIMETHICONE; DIMETHICONE/VINYL DIMETHICONE CROSSPOLYMER (SOFT PARTICLE); GLYCYRRHIZA URALENSIS; SUNFLOWER OIL; CENTELLA ASIATICA LEAF; ECKLONIA KUROME

ZO® Skin Health Sunscreen + Primer Broad-Spectrum SPF 30
National Drug Codes: 42851-060-15, 42851-060-30, and 42851-060-75

Drug Facts

ACTIVE INGREDIENT

Active Ingredients | Purpose
Titanium Dioxide 1.0% | Sunscreen
Zinc Oxide 20.0% | Sunscreen

Uses

- helps prevent sunburn
- if used as directed with other sun protection measures (see Directions), decreases the risk of skin cancer and early skin aging caused by the sun

Warnings

For external use only.

Do not use

- on damaged or broken skin.

When using this product

- keep out of eyes. Rinse with water to remove.

Stop use and ask a doctor if

- rash occurs.

Keep out of reach of children.

- If swallowed, get medical help or contact a Poison Control Center right away.

Directions

- Apply liberally 15 minutes before sun exposure and as needed.
- Use a water-resistant sunscreen if swimming or sweating.
- Reapply at least every 2 hours.
- Children under 6 months: Ask a doctor.
- Sun Protection Measures. Spending time in the sun increases your risk of skin cancer and early skin aging. To decrease this risk, regularly use a sunscreen with a broad-spectrum SPF value of 15 or higher and other sun protection measures including:
  - limit time in the sun, especially from 10 a.m.– 2 p.m.
- wear long-sleeved shirts, pants, hats, and sunglasses.

Other Information

- Protect this product from excessive heat and direct sun.

Inactive Ingredients

Cyclopentasiloxane, Dimethicone, Dimethicone Crosspolymer, PEG-10 Dimethicone, Phenyl Trimethicone,Dimethicone/Vinyl DimethiconeCrosspolymer, Glycyrrhiza Uralensis (Licorice) Root Extract, Helianthus Annuus (Sunflower) Seed Oil, Centella Asiatica Extract, Ecklonia Kurome Extract, Glycine Soja (Soybean) Seed Extract, Rosmarinus Officinalis (Rosemary) Leaf Extract,
Hexyl Laurate, Polyglyceryl-4 Isostearate, Tribehenin, Bisabolol, Cetyl PEG/PPG-10/1 Dimethicone,Water, Glycerin, Squalane, Polymethyl Methacrylate, Dimethiconol, Caprylic/Capric Triglyceride, Stearic Acid, Alumina, Caprylyl Glycol, Behenyl Behenate, Melanin, Tocopheryl Acetate, Ethyl Ferulate, Triethoxycaprylylsilane, Ascorbic Acid, Retinyl Palmitate, Ethylhexylglycerin, Tocopherol,
Myristoyl Pentapeptide-8, Pentylene Glycol, Phenoxyethanol, Chlorphenesin, Iron Oxides.

Dist. by ZO Skin Health, Inc. Irvine, CA 92618

Changes to: Uses, Directions

Addition of: if used as directed with other sun protection measures (see Directions), decreases the risk of skin cancer and early skin aging caused by the sun

Changed formatting of Directions.

PRINCIPAL DISPLAY PANEL - 30 mL Bottle Carton

ZO® SKIN HEALTH
BY ZEIN OBAGI MD

NDC 42851-060-30

SUNSCREEN + PRIMER
BROAD-SPECTRUM
SPF 30

ZOX^12™

30 mL / 1 Fl. Oz.